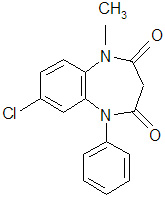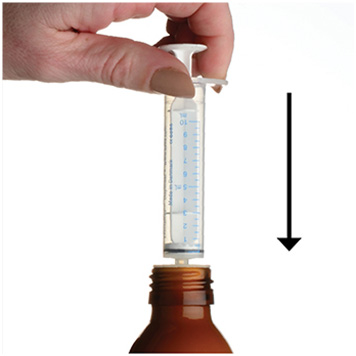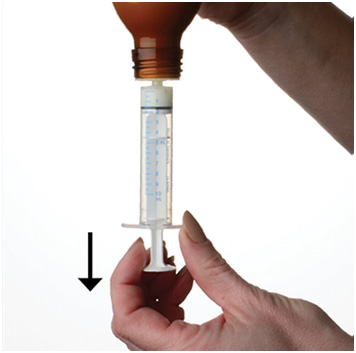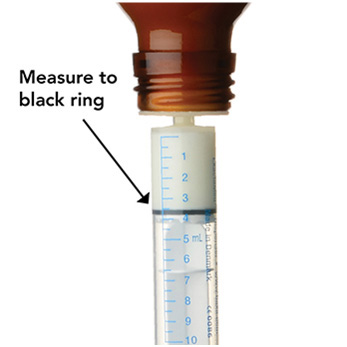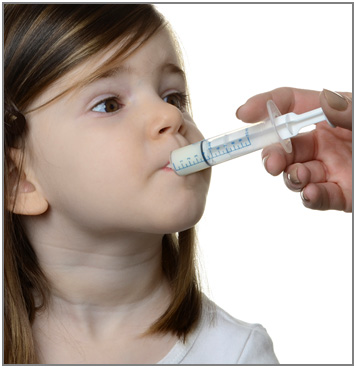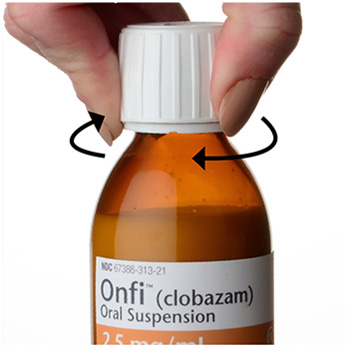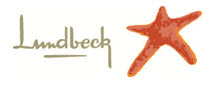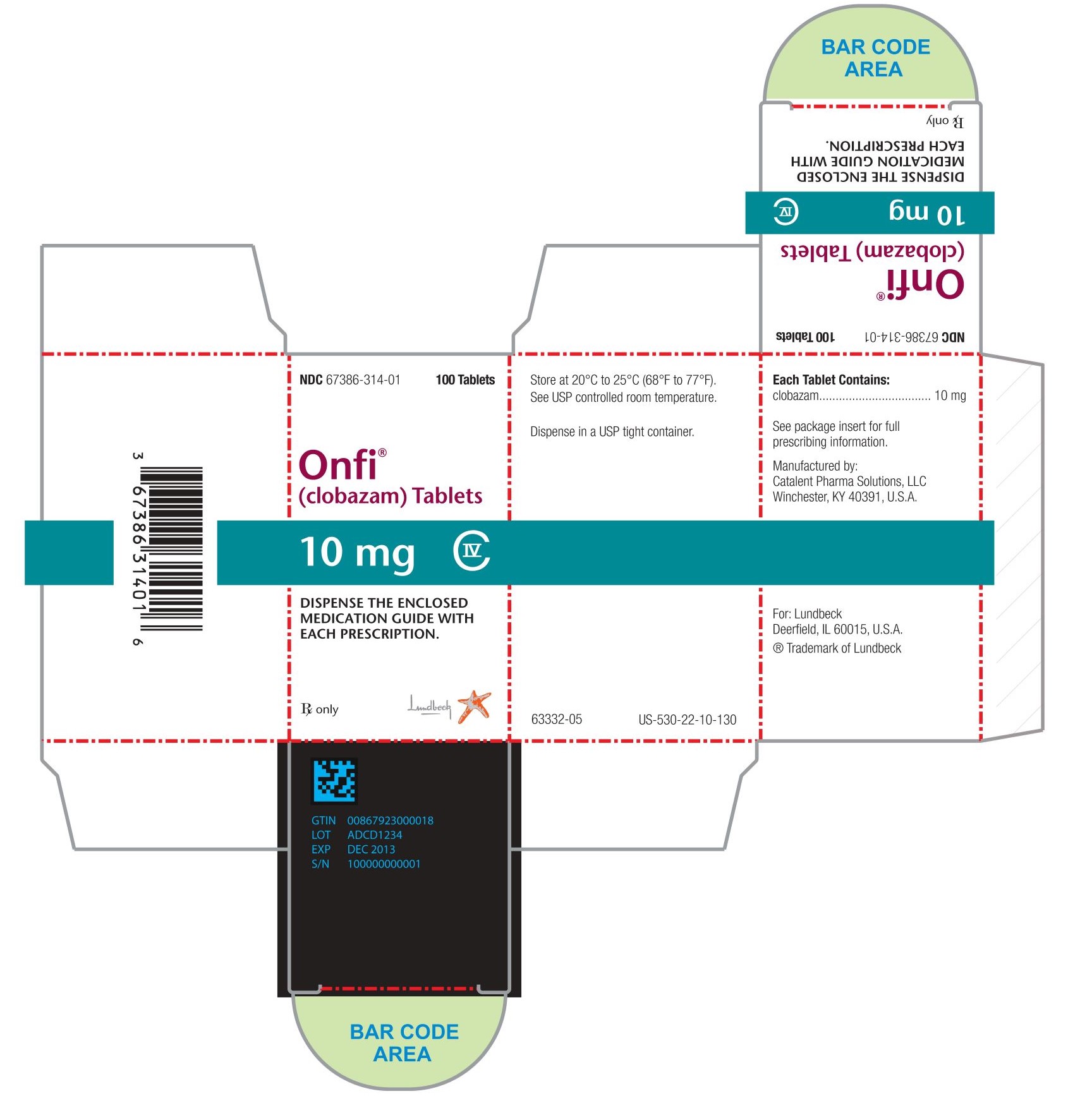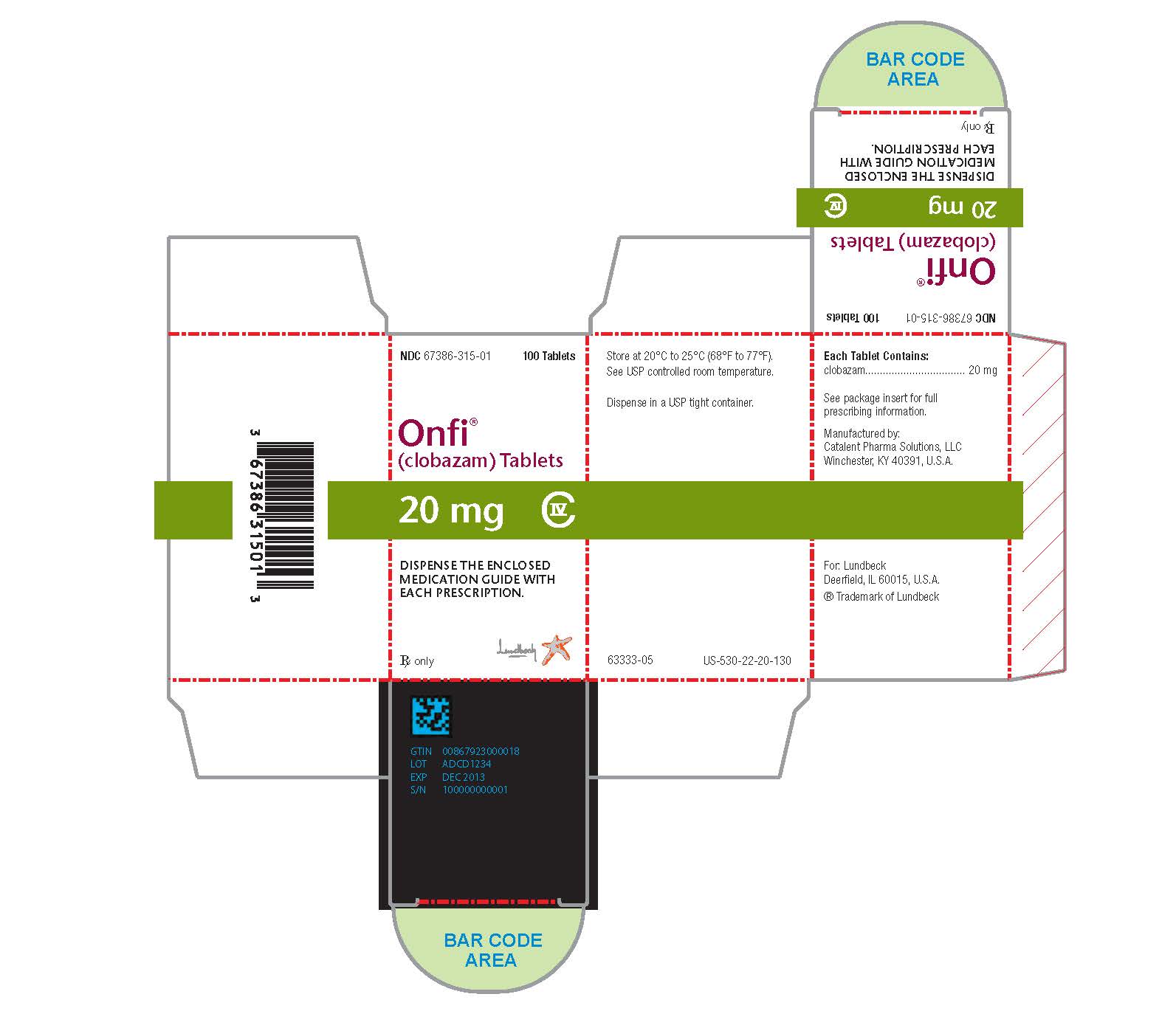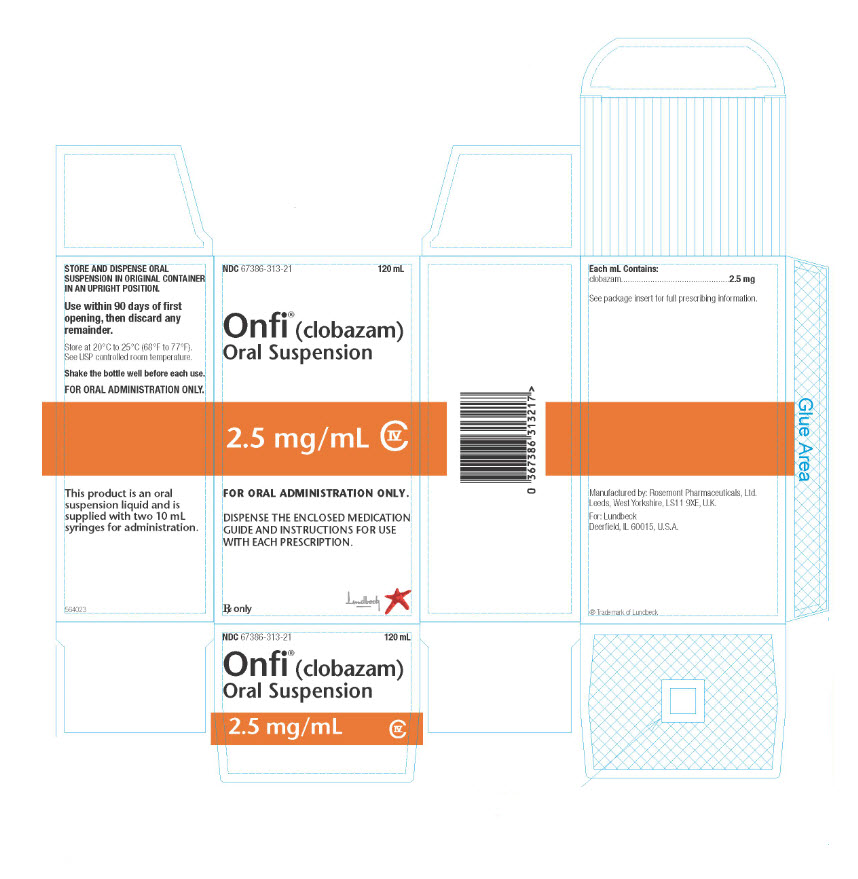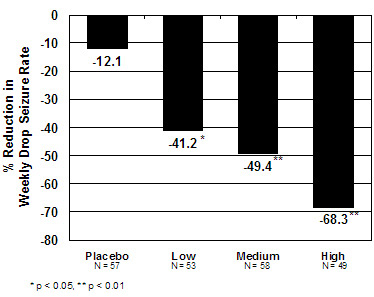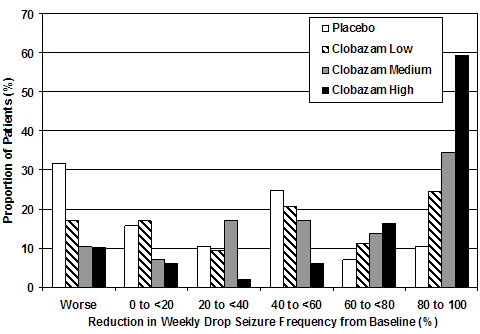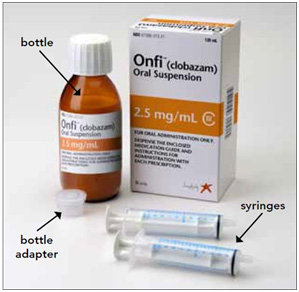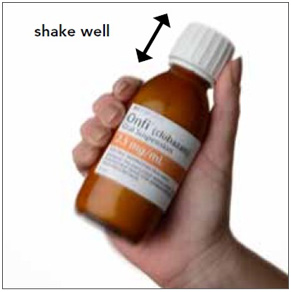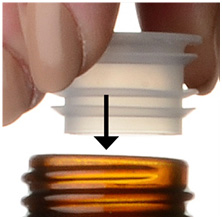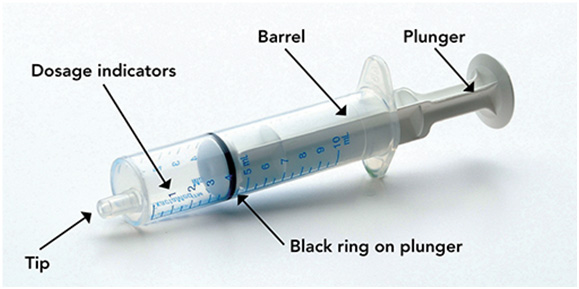 DRUG LABEL: Onfi
NDC: 67386-314 | Form: TABLET
Manufacturer: Lundbeck Pharmaceuticals LLC
Category: prescription | Type: HUMAN PRESCRIPTION DRUG LABEL
Date: 20240312
DEA Schedule: CIV

ACTIVE INGREDIENTS: CLOBAZAM 10 mg/1 1
INACTIVE INGREDIENTS: STARCH, CORN; LACTOSE MONOHYDRATE; MAGNESIUM STEARATE; SILICON DIOXIDE; TALC

HIGHLIGHTS OF PRESCRIBING INFORMATION

These highlights do not include all the information needed to use ONFI safely and effectively. See full prescribing information for ONFI.
ONFI® (clobazam) tablets, for oral use, CIV
ONFI® (clobazam) oral suspension, CIV
Initial U.S. Approval: 2011

WARNING: RISKS FROM CONCOMITANT USE WITH OPIOIDS; ABUSE, MISUSE, AND ADDICTION; and DEPENDENCE AND WITHDRAWAL REACTIONS

See full prescribing information for complete boxed warning.

- Concomitant use of benzodiazepines and opioids may result in profound sedation, respiratory depression, coma, and death. Reserve concomitant prescribing of these drugs for patients for whom alternative treatment options are inadequate. Limit dosages and durations to the minimum required. Follow patients for signs and symptoms of respiratory depression and sedation (5.1, 7.1).
- The use of benzodiazepines, including ONFI, exposes users to risks of abuse, misuse, and addiction, which can lead to overdose or death. Before prescribing ONFI and throughout treatment, assess each patient’s risk for abuse, misuse, and addiction (5.2).
- Abrupt discontinuation or rapid dosage reduction of ONFI after continued use may precipitate acute withdrawal reactions, which can be life-threatening. To reduce the risk of withdrawal reactions, use a gradual taper to discontinue ONFI or reduce the dosage (2.2, 5.3).

RECENT MAJOR CHANGES

- Warnings and Precautions (5.7) 3/2024

1 INDICATIONS AND USAGE

ONFI is a benzodiazepine indicated for adjunctive treatment of seizures associated with Lennox-Gastaut syndrome (LGS) in patients 2 years of age or older (1)

2 DOSAGE AND ADMINISTRATION

- For doses above 5 mg/day administer in two divided doses (2.1)
- Patients ≤30 kg body weight: Initiate at 5 mg daily and titrate as tolerated up to 20 mg daily (2.1)
- Patients >30 kg body weight: Initiate at 10 mg daily and titrate as tolerated up to 40 mg daily (2.1)
- Dosage adjustment needed in following groups:
  - Geriatric patients (2.4, 8.5)
  - Known CYP2C19 poor metabolizers (2.5)
  - Mild or moderate hepatic impairment; no information for severe hepatic impairment (2.7, 8.8)
- Tablets: Administer whole, broken in half along the score, or crush and mix in applesauce (2.3)
- Measure prescribed amount of oral suspension using provided adapter and dosing syringe (2.3)
- Tablets and Oral suspension: Can be taken with or without food (2.3)

3 DOSAGE FORMS AND STRENGTHS

- Tablet: 10 mg and 20 mg with a functional score (3)
- Oral Suspension: 2.5 mg/mL in 120 mL bottles (3)

4 CONTRAINDICATIONS

History of hypersensitivity to the drug or its ingredients (4)

5 WARNINGS AND PRECAUTIONS

- Somnolence or Sedation: Monitor for central nervous system (CNS) depression. Risk may be increased with concomitant use of other CNS depressants (5.4, 5.5)
- Serious Dermatological Reactions (including Stevens-Johnson syndrome and toxic epidermal necrolysis): Discontinue ONFI at first sign of rash unless the rash is clearly not drug-related (5.6)
- Drug Reaction with Eosinophilia and Systemic Symptoms (DRESS)/Multiorgan Hypersensitivity: Discontinue if no alternative etiology (5.7)
- Suicidal Behavior and Ideation: Monitor for suicidal thoughts or behaviors (5.8)
- Neonatal Sedation and Withdrawal Syndrome: ONFI use during pregnancy can result in neonatal sedation and/or neonatal withdrawal (5.9,8.1)

6 ADVERSE REACTIONS

Adverse reactions that occurred at least 10% more frequently than placebo in any ONFI dose included constipation, somnolence or sedation, pyrexia, lethargy, and drooling (6.1)

To report SUSPECTED ADVERSE REACTIONS, contact Lundbeck at 1-800-455-1141 or FDA at 1-800-FDA-1088 or www.fda.gov/medwatch.

7 DRUG INTERACTIONS

- Alcohol: Increases blood levels of clobazam by about 50% (7.2)
- Drugs metabolized by CYP2D6: Lower doses of these drugs may be required when used concomitantly with ONFI (7.3)
- Strong or Moderate CYP2C19 Inhibitors: Dosage adjustment of ONFI may be necessary (7.4)

8 USE IN SPECIFIC POPULATIONS

Pregnancy: Based on animal data, may cause fetal harm (8.1)

FULL PRESCRIBING INFORMATION

WARNING: RISKS FROM CONCOMITANT USE WITH OPIOIDS; ABUSE, MISUSE, AND ADDICTION; and DEPENDENCE AND WITHDRAWAL REACTIONS

- Concomitant use of benzodiazepines and opioids may result in profound sedation, respiratory depression, coma, and death. Reserve concomitant prescribing of these drugs for patients for whom alternative treatment options are inadequate. Limit dosages and durations to the minimum required. Follow patients for signs and symptoms of respiratory depression and sedation [see Warnings and Precautions (5.1), Drug Interactions (7.1)].
- The use of benzodiazepines, including ONFI, exposes users to risks of abuse, misuse, and addiction, which can lead to overdose or death. Abuse and misuse of benzodiazepines commonly involve concomitant use of other medications, alcohol, and/or illicit substances, which is associated with an increased frequency of serious adverse outcomes. Before prescribing ONFI and throughout treatment, assess each patient’s risk for abuse, misuse, and addiction [see Warnings and Precautions (5.2)].
- The continued use of benzodiazepines, including ONFI, may lead to clinically significant physical dependence. The risks of dependence and withdrawal increase with longer treatment duration and higher daily dose. Abrupt discontinuation or rapid dosage reduction of ONFI after continued use may precipitate acute withdrawal reactions, which can be life-threatening. To reduce the risk of withdrawal reactions, use a gradual taper to discontinue ONFI or reduce the dosage [see Dosage and Administration (2.2) and Warnings and Precautions (5.3)].

1 INDICATIONS AND USAGE

ONFI® (clobazam) is indicated for the adjunctive treatment of seizures associated with Lennox-Gastaut syndrome (LGS) in patients 2 years of age or older.

2 DOSAGE AND ADMINISTRATION

2.1 Dosing Information

A daily dose of ONFI greater than 5 mg should be administered in divided doses twice daily; a 5 mg daily dose can be administered as a single dose. Dose patients according to body weight. Individualize dosing within each body weight group, based on clinical efficacy and tolerability. Each dose in Table 1 (e.g., 5 to 20 mg in ≤30 kg weight group) has been shown to be effective, although effectiveness increases with increasing dose [see Clinical Studies (14)]. Do not proceed with dose escalation more rapidly than weekly, because serum concentrations of clobazam and its active metabolite require 5 and 9 days, respectively, to reach steady-state.

Table 1. Recommended Total Daily Dosing by Weight Group
 | ≤30 kg Body Weight | >30 kg Body Weight
Starting Dose | 5 mg | 10 mg
Starting Day 7 | 10 mg | 20 mg
Starting Day 14 | 20 mg | 40 mg

2.2 Discontinuation or Dosage Reduction of ONFI

To reduce the risk of withdrawal reactions, increased seizure frequency, and status epilepticus, use a gradual taper to discontinue ONFI or reduce the dosage. Taper by decreasing the total daily dose by 5-10 mg/day on a weekly basis until discontinued. If a patient develops withdrawal reactions, consider pausing the taper or increasing the dosage to the previous tapered dosage level. Subsequently decrease the dosage more slowly [see Warnings and Precautions (5.3) and Drug Abuse and Dependence (9.3)].

2.3 Important Administration Instructions

Instruct patients to read the "Instructions for Use" carefully for complete directions on how to properly dose and administer ONFI oral suspension.

ONFI Tablet Oral Administration
ONFI tablets can be taken with or without food.
ONFI tablets can be administered whole, broken in half along the score, or crushed and mixed in applesauce.

ONFI Oral Suspension Oral Administration
ONFI oral suspension can be taken with or without food [see Clinical Pharmacology (12.3)].

Shake ONFI Oral Suspension well before every administration. When administering the oral suspension, use only the oral dosing syringe provided with the product. Each carton includes two syringes, but only one syringe should be used for dosing. The second oral syringe is reserved as a replacement in case the first syringe is damaged or lost. Insert the provided adapter firmly into the neck of the bottle before first use and keep the adapter in place for the duration of the usage of the bottle. To withdraw the dose, insert the dosing syringe into the adapter and invert the bottle then slowly pull back the plunger to prescribed dose. After removing the syringe from the bottle adapter, slowly squirt ONFI Oral Suspension into the corner of the patient's mouth. Replace the cap after each use. The cap fits over the adapter when the adapter is properly placed. See ONFI Oral Suspension "Instructions for Use" for complete instruction on how to properly dose and administer the ONFI Oral Suspension.

2.4 Dosage Adjustments in Geriatric Patients

Plasma concentrations at any given dose are generally higher in the elderly: proceed slowly with dose escalation. The starting dose should be 5 mg/day for all elderly patients. Then titrate elderly patients according to weight, but to half the dose presented in Table 1, as tolerated. If necessary and based upon clinical response, an additional titration to the maximum dose (20 mg/day or 40 mg/day, depending on weight) may be started on day 21 [see Use in Specific Populations (8.5)].

2.5 Dosage Adjustments in CYP2C19 Poor Metabolizers

In CYP2C19 poor metabolizers, levels of N-desmethylclobazam, clobazam's active metabolite, will be increased. Therefore, in patients known to be CYP2C19 poor metabolizers, the starting dose should be 5 mg/day and dose titration should proceed slowly according to weight, but to half the dose presented in Table 1, as tolerated. If necessary and based upon clinical response, an additional titration to the maximum dose (20 mg/day or 40 mg/day, depending on the weight group) may be started on day 21 [see Use in Specific Populations (8.6), Clinical Pharmacology (12.5)].

2.6 Patients with Renal Impairment

No dose adjustment is required for patients with mild and moderate renal impairment. There is no experience with ONFI in patients with severe renal impairment or end stage renal disease (ESRD). It is not known if clobazam or its active metabolite, N-desmethylclobazam, is dialyzable [see Use in Specific Populations (8.7), Clinical Pharmacology (12.3)].

2.7 Dosage Adjustments in Patients with Hepatic Impairment

ONFI is hepatically metabolized; however, there are limited data to characterize the effect of hepatic impairment on the pharmacokinetics of ONFI. For this reason, proceed slowly with dosing escalations. For patients with mild to moderate hepatic impairment (Child-Pugh score 5-9), the starting dose should be 5 mg/day in both weight groups. Then titrate patients according to weight, but to half the dose presented in Table 1, as tolerated. If necessary and based upon clinical response, start an additional titration on day 21 to the maximum dose (20 mg/day or 40 mg/day, depending on the weight group). There is inadequate information about metabolism of ONFI in patients with severe hepatic impairment. Therefore no dosing recommendation in those patients can be given [see Use in Specific Populations (8.8), Clinical Pharmacology (12.3)].

3 DOSAGE FORMS AND STRENGTHS

Tablets: 10 mg and 20 mg with a functional score for oral administration.
Each ONFI tablet is a white to off-white, oval tablet with a functional score on one side and either a "1" and "0" or a "2" and "0" debossed on the other side.

Oral Suspension: 2.5 mg/mL for oral administration. Each bottle contains 120 mL of an off-white suspension.

4 CONTRAINDICATIONS

ONFI is contraindicated in patients with a history of hypersensitivity to the drug or its ingredients. Hypersensitivity reactions have included serious dermatological reactions [see Warnings and Precautions (5.6, 5.7)].

5 WARNINGS AND PRECAUTIONS

5.1 Risks from Concomitant Use with Opioids

Concomitant use of benzodiazepines, including ONFI, and opioids may result in profound sedation, respiratory depression, coma, and death. Because of these risks, reserve concomitant prescribing of benzodiazepines and opioids for patients for whom alternative treatment options are inadequate.

Observational studies have demonstrated that concomitant use of opioid analgesics and benzodiazepines increases the risk of drug-related mortality compared to use of opioids alone. If a decision is made to prescribe ONFI concomitantly with opioids, prescribe the lowest effective dosages and minimum durations of concomitant use, and follow patients closely for signs and symptoms of respiratory depression and sedation. Advise both patients and caregivers about the risks of respiratory depression and sedation when ONFI is used with opioids [see Drug Interactions (7.1)].

5.2 Abuse, Misuse, and Addiction

The use of benzodiazepines, including ONFI, exposes users to the risks of abuse, misuse, and addiction, which can lead to overdose or death. Abuse and misuse of benzodiazepines often (but not always) involve the use of doses greater than the maximum recommended dosage and commonly involve concomitant use of other medications, alcohol, and/or illicit substances, which is associated with an increased frequency of serious adverse outcomes, including respiratory depression, overdose, or death [see Drug Abuse and Dependence (9.2)].

Before prescribing ONFI and throughout treatment, assess each patient’s risk for abuse, misuse, and addiction (e.g., using a standardized screening tool). Use of ONFI, particularly in patients at elevated risk, necessitates counseling about the risks and proper use of ONFI along with monitoring for signs and symptoms of abuse, misuse, and addiction. Prescribe the lowest effective dosage; avoid or minimize concomitant use of CNS depressants and other substances associated with abuse, misuse, and addiction (e.g., opioid analgesics, stimulants); and advise patients on the proper disposal of unused drug. If a substance use disorder is suspected, evaluate the patient and institute (or refer them for) early treatment, as appropriate.

5.3 Dependence and Withdrawal Reactions

To reduce the risk of withdrawal reactions, use a gradual taper to discontinue ONFI or reduce the dosage [see Dosage and Administration (2.2)].

Patients at an increased risk of withdrawal adverse reactions after benzodiazepine discontinuation or rapid dosage reduction include those who take higher dosages, and those who have had longer durations of use.

Acute Withdrawal Reactions

The continued use of benzodiazepines, including ONFI, may lead to clinically significant physical dependence. Abrupt discontinuation or rapid dosage reduction of ONFI after continued use, or administration of flumazenil (a benzodiazepine antagonist) may precipitate acute withdrawal reactions, which can be life-threatening (e.g., seizures) [see Drug Abuse and Dependence (9.3)].

Protracted Withdrawal Syndrome

In some cases, benzodiazepine users have developed a protracted withdrawal syndrome with withdrawal symptoms lasting weeks to more than 12 months [see Drug Abuse and Dependence (9.3)].

5.4 Potentiation of Sedation from Concomitant Use with Central Nervous System Depressants

Since ONFI has a central nervous system (CNS) depressant effect, patients or their caregivers should be cautioned against simultaneous use with other CNS depressant drugs or alcohol, and cautioned that the effects of other CNS depressant drugs or alcohol may be potentiated [see Drug Interactions (7.2)].

5.5 Somnolence or Sedation

ONFI causes somnolence and sedation. In clinical trials, somnolence or sedation was reported at all effective doses and was dose-related.

In general, somnolence and sedation begin within the first month of treatment and may diminish with continued treatment. Prescribers should monitor patients for somnolence and sedation, particularly with concomitant use of other central nervous system depressants. Prescribers should caution patients against engaging in hazardous activities requiring mental alertness, such as operating dangerous machinery or motor vehicles, until the effect of ONFI is known.

5.6 Serious Dermatological Reactions

Serious skin reactions, including Stevens-Johnson syndrome (SJS) and toxic epidermal necrolysis (TEN), have been reported with ONFI in both children and adults during the postmarketing period. Patients should be closely monitored for signs or symptoms of SJS/TEN, especially during the first 8 weeks of treatment initiation or when re-introducing therapy. ONFI should be discontinued at the first sign of rash, unless the rash is clearly not drug-related. If signs or symptoms suggest SJS/TEN, use of this drug should not be resumed and alternative therapy should be considered [see Contraindications (4)].

5.7 Drug Reaction with Eosinophilia and Systemic Symptoms (DRESS)/Multiorgan Hypersensitivity

Drug Reaction with Eosinophilia and Systemic Symptoms (DRESS), also known as multiorgan hypersensitivity, has been reported in patients taking antiepileptic drugs, including ONFI. These events can be fatal or life-threatening, particularly if diagnosis and treatment do not occur as early as possible. DRESS typically, although not exclusively, presents with fever, rash, lymphadenopathy, and/or facial swelling, in association with other organ system involvement, such as hepatitis, nephritis, hematological abnormalities, myocarditis, or myositis, sometimes resembling an acute viral infection. Eosinophilia is often present. Because this disorder is variable in its expression, other organ systems not noted here may be involved. It is important to note that early manifestations of hypersensitivity, such as fever or lymphadenopathy, may be present even though rash is not evident. If such signs or symptoms are present, the patient should be evaluated immediately. ONFI should be discontinued if an alternative etiology for the signs or symptoms cannot be established [see Contraindications (4)].

5.8 Suicidal Behavior and Ideation

Antiepileptic drugs (AEDs), including ONFI, increase the risk of suicidal thoughts or behavior in patients taking these drugs for any indication. Patients treated with any AED for any indication should be monitored for the emergence or worsening of depression, suicidal thoughts or behavior, and/or any unusual changes in mood or behavior.

Pooled analyses of 199 placebo-controlled clinical trials (mono- and adjunctive therapy) of 11 different AEDs showed that patients randomized to one of the AEDs had approximately twice the risk (adjusted relative risk 1.8, 95% confidence interval [CI]: 1.2, 2.7) of suicidal thinking or behavior compared to patients randomized to placebo. In these trials, which had a median treatment duration of 12 weeks, the estimated incidence rate of suicidal behavior or ideation among 27,863 AED-treated patients was 0.43%, compared to 0.24% among 16,029 placebo-treated patients, representing an increase of approximately one case of suicidal thinking or behavior for every 530 patients treated. There were four suicides in drug-treated patients in the trials and none in placebo-treated patients, but the number is too small to allow any conclusion about drug effect on suicide.

The increased risk of suicidal thoughts or behavior with AEDs was observed as early as one week after starting drug treatment with AEDs and persisted for the duration of treatment assessed. Because most trials included in the analysis did not extend beyond 24 weeks, the risk of suicidal thoughts or behavior beyond 24 weeks could not be assessed.

The risk of suicidal thoughts or behavior was generally consistent among drugs in the data analyzed. The finding of increased risk with AEDs of varying mechanisms of action and across a range of indications suggests that the risk applies to all AEDs used for any indication. The risk did not vary substantially by age (5-100 years) in the clinical trials analyzed. Table 2 shows absolute and relative risk by indication for all evaluated AEDs.

Table 2. Risk by Indication for Antiepileptic Drugs in the Pooled Analysis
Indication | Placebo Patients with Events per 1000 Patients | Drug Patients with Events per 1000 Patients | Relative Risk: Incidence of Drug Events in Drug Patients/Incidence in Placebo Patients | Risk Difference: Additional Drug Patients with Events per 1000 Patients
Epilepsy | 1.0 | 3.4 | 3.5 | 2.4
Psychiatric | 5.7 | 8.5 | 1.5 | 2.9
Other | 1.0 | 1.8 | 1.9 | 0.9
Total | 2.4 | 4.3 | 1.8 | 1.9

The relative risk for suicidal thoughts or behavior was higher in clinical trials for epilepsy than in clinical trials for psychiatric or other conditions, but the absolute risk differences were similar for the epilepsy and psychiatric indications.

Anyone considering prescribing ONFI or any other AED must balance the risk of suicidal thoughts or behavior with the risk of untreated illness. Epilepsy and many other illnesses for which AEDs are prescribed are themselves associated with morbidity and mortality and an increased risk of suicidal thoughts and behavior. Should suicidal thoughts and behavior emerge during treatment, the prescriber needs to consider whether the emergence of these symptoms in any given patient may be related to the illness being treated.

Patients, their caregivers, and families should be informed that AEDs increase the risk of suicidal thoughts and behavior and should be advised of the need to be alert for the emergence or worsening of the signs and symptoms of depression, any unusual changes in mood or behavior, or the emergence of suicidal thoughts, behavior, or thoughts about self-harm. Behaviors of concern should be reported immediately to healthcare providers.

5.9 Neonatal Sedation and Withdrawal Syndrome

Use of ONFI late in pregnancy can result in sedation (respiratory depression, lethargy, hypotonia) and/or withdrawal symptoms (hyperreflexia, irritability, restlessness, tremors, inconsolable crying, and feeding difficulties) in the neonate [see Use in Specific Populations (8.1)]. Monitor neonates exposed to ONFI during pregnancy or labor for signs of sedation and monitor neonates exposed to ONFI during pregnancy for signs of withdrawal; manage these neonates accordingly.

6 ADVERSE REACTIONS

Clinically significant adverse reactions that appear in other sections of the labeling include the following:

- Risks from Concomitant Use with Opioids [see Warnings and Precautions (5.1)]
- Abuse, Misuse, and Addiction [see Warnings and Precautions (5.2)]
- Dependence and Withdrawal Reactions [see Warnings and Precautions (5.3)]
- Potentiation of Sedation from Concomitant Use with Central Nervous System Depressants [see Warnings and Precautions (5.4)]
- Somnolence or Sedation [see Warnings and Precautions (5.5)]
- Serious Dermatological Reactions [see Contraindications (4), Warnings and Precautions (5.6)]
- Drug Reaction with Eosinophilia and Systemic Symptoms (DRESS)/Multiorgan Hypersensitivity [see Warnings and Precautions (5.7)]
- Suicidal Behavior and Ideation [see Warnings and Precautions (5.8)]
- Neonatal Sedation and Withdrawal Syndrome [see Warnings and Precautions (5.9)]

6.1 Clinical Trials Experience

Because clinical trials are conducted under widely varying conditions, adverse reaction rates observed in the clinical trials of a drug cannot be directly compared to rates in the clinical trials of another drug and may not reflect the rates observed in practice.

During its development for the adjunctive treatment of seizures associated with LGS, ONFI was administered to 333 healthy volunteers and 300 patients with a current or prior diagnosis of LGS, including 197 patients treated for 12 months or more. The conditions and duration of exposure varied greatly and included single- and multiple-dose clinical pharmacology studies in healthy volunteers and two double-blind studies in patients with LGS (Study 1 and 2) [see Clinical Studies (14)]. Only Study 1 included a placebo group, allowing comparison of adverse reaction rates on ONFI at several doses to placebo.

Adverse Reactions Leading to Discontinuation in an LGS Placebo Controlled Clinical Trial (Study 1)
The adverse reactions associated with ONFI treatment discontinuation in ≥1% of patients in decreasing order of frequency included lethargy, somnolence, ataxia, aggression, fatigue, and insomnia.

Most Common Adverse Reactions in an LGS Placebo Controlled Clinical Trial (Study 1)
Table 3 lists the adverse reactions that occurred in ≥5% of ONFI-treated patients (at any dose), and at a rate greater than placebo-treated patients, in the randomized, double-blind, placebo-controlled, parallel group clinical study of adjunctive AED therapy for 15 weeks (Study 1).

Table 3. Adverse Reactions Reported for ≥5% of Patients and More Frequently than Placebo in Any Treatment Group
 | Placebo N=59 % | ONFI Dose Level |  |  | All ONFI N=179 %
 | Placebo N=59 % | Lowa N=58 % | Mediumb N=62 % | Highc N=59 % | All ONFI N=179 %
Gastrointestinal Disorders
Vomiting | 5 | 9 | 5 | 7 | 7
Constipation | 0 | 2 | 2 | 10 | 5
Dysphagia | 0 | 0 | 0 | 5 | 2
General Disorders and Administration Site Conditions
Pyrexia | 3 | 17 | 10 | 12 | 13
Irritability | 5 | 3 | 11 | 5 | 7
Fatigue | 2 | 5 | 5 | 3 | 5
Infections and Infestations
Upper respiratory tract infection | 10 | 10 | 13 | 14 | 12
Pneumonia | 2 | 3 | 3 | 7 | 4
Urinary tract infection | 0 | 2 | 5 | 5 | 4
Bronchitis | 0 | 2 | 0 | 5 | 2
Metabolism and Nutrition Disorders
Decreased appetite | 3 | 3 | 0 | 7 | 3
Increased appetite | 0 | 2 | 3 | 5 | 3
Nervous System Disorders
Somnolence or Sedation | 15 | 17 | 27 | 32 | 26
Somnolence | 12 | 16 | 24 | 25 | 22
Sedation | 3 | 2 | 3 | 9 | 5
Lethargy | 5 | 10 | 5 | 15 | 10
Drooling | 3 | 0 | 13 | 14 | 9
Ataxia | 3 | 3 | 2 | 10 | 5
Psychomotor hyperactivity | 3 | 3 | 3 | 5 | 4
Dysarthria | 0 | 2 | 2 | 5 | 3
Psychiatric Disorders
Aggression | 5 | 3 | 8 | 14 | 8
Insomnia | 2 | 2 | 5 | 7 | 5
Respiratory Disorders
Cough | 0 | 3 | 5 | 7 | 5
aMaximum daily dose of 5 mg for ≤30 kg body weight; 10 mg for >30 kg body weight
bMaximum daily dose of 10 mg for ≤30 kg body weight; 20 mg for >30 kg body weight
cMaximum daily dose of 20 mg for ≤30 kg body weight; 40 mg for >30 kg body weight

6.2 Postmarketing Experience

These reactions are reported voluntarily from a population of uncertain size; therefore, it is not possible to estimate their frequency or establish a causal relationship to drug exposure. Adverse reactions are categorized by system organ class.

Blood Disorders: Anemia, eosinophilia, leukopenia, thrombocytopenia
Eye Disorders: Diplopia, vision blurred
Gastrointestinal Disorders: Abdominal distention
General Disorders and Administration Site Conditions: Hypothermia
Investigations: Hepatic enzyme increased
Musculoskeletal: Muscle spasms
Psychiatric Disorders: Agitation, anxiety, apathy, confusional state, depression, delirium, delusion, hallucination
Renal and Urinary Disorders: Urinary retention
Respiratory Disorders: Aspiration, respiratory depression
Skin and Subcutaneous Tissue Disorders: Rash, urticaria, angioedema, and facial and lip edema

7 DRUG INTERACTIONS

7.1 Opioids

The concomitant use of benzodiazepines and opioids increases the risk of respiratory depression because of actions at different receptor sites in the CNS that control respiration. Benzodiazepines interact at GABAA sites, and opioids interact primarily at mu receptors. When benzodiazepines and opioids are combined, the potential for benzodiazepines to significantly worsen opioid-related respiratory depression exists. Limit dosage and duration of concomitant use of benzodiazepines and opioids, and follow patients closely for respiratory depression and sedation [see Warnings and Precautions (5.1)].

7.2 CNS Depressants and Alcohol

Concomitant use of ONFI with other CNS depressants may increase the risk of sedation and somnolence [see Warnings and Precautions (5.4)].

Alcohol, as a CNS depressant, will interact with ONFI in a similar way and also increases clobazam's maximum plasma exposure by approximately 50%. Therefore, caution patients or their caregivers against simultaneous use with other CNS depressant drugs or alcohol, and caution that the effects of other CNS depressant drugs or alcohol may be potentiated [see Warnings and Precautions (5.4)].

7.3 Effect of ONFI on Other Drugs

Hormonal Contraceptives
ONFI is a weak CYP3A4 inducer. As some hormonal contraceptives are metabolized by CYP3A4, their effectiveness may be diminished when given with ONFI. Additional non-hormonal forms of contraception are recommended when using ONFI [see Clinical Pharmacology (12.3), Patient Counseling Information (17)].

Drugs Metabolized by CYP2D6
ONFI inhibits CYP2D6. Dose adjustment of drugs metabolized by CYP2D6 may be necessary [see Clinical Pharmacology (12.3)].

7.4 Effect of Other Drugs on ONFI

Strong and moderate inhibitors of CYP2C19
Strong and moderate inhibitors of CYP2C19 may result in increased exposure to N-desmethylclobazam, the active metabolite of clobazam. This may increase the risk of dose-related adverse reactions. Dosage adjustment of ONFI may be necessary when co-administered with strong CYP2C19 inhibitors (e.g., fluconazole, fluvoxamine, ticlopidine) or moderate CYP2C19 inhibitors (e.g., omeprazole) [see Clinical Pharmacology (12.3)].

8 USE IN SPECIFIC POPULATIONS

8.1 Pregnancy

Pregnancy Registry
There is a pregnancy exposure registry that monitors pregnancy outcomes in women exposed to AEDs, such as ONFI, during pregnancy. Healthcare providers are encouraged to recommend that pregnant women taking ONFI enroll in the North American Antiepileptic Drug (NAAED) Pregnancy Registry by calling 1-888-233-2334 or online at http://www.aedpregnancyregistry.org/.

Risk Summary
Neonates born to mothers using benzodiazepines late in pregnancy have been reported to experience symptoms of sedation and/or neonatal withdrawal [see Warnings and Precautions (5.9) and Clinical Considerations]. Available data from published observational studies of pregnant women exposed to benzodiazepines do not report a clear association with benzodiazepines and major birth defects (see Data).

Administration of clobazam to pregnant rats and rabbits during the period of organogenesis or to rats throughout pregnancy and lactation resulted in developmental toxicity, including increased incidences of fetal malformations and mortality, at plasma exposures for clobazam and its major active metabolite, N-desmethylclobazam, below those expected at therapeutic doses in patients [see Animal Data]. Data for other benzodiazepines suggest the possibility of long-term effects on neurobehavioral and immunological function in animals following prenatal exposure to benzodiazepines at clinically relevant doses. ONFI should be used during pregnancy only if the potential benefit to the mother justifies the potential risk to the fetus. Advise a pregnant woman and women of childbearing age of the potential risk to a fetus.

The background risk of major birth defects and miscarriage for the indicated population is unknown. All pregnancies have a background risk of birth defect, loss, or other adverse outcomes. In the U.S. general population, the estimated background risk of major birth defects and of miscarriage in clinically recognized pregnancies is 2-4% and 15-20%, respectively.

Clinical Considerations
Fetal/Neonatal Adverse Reactions
Benzodiazepines cross the placenta and may produce respiratory depression, hypotonia, and sedation in neonates. Monitor neonates exposed to ONFI during pregnancy or labor for signs of sedation, respiratory depression, hypotonia, and feeding problems. Monitor neonates exposed to ONFI during pregnancy for signs of withdrawal. Manage these neonates accordingly [see Warnings and Precautions (5.9)].

Data
Human Data
Published data from observational studies on the use of benzodiazepines during pregnancy do not report a clear association with benzodiazepines and major birth defects. Although early studies reported an increased risk of congenital malformations with diazepam and chlordiazepoxide, there was no consistent pattern noted. In addition, the majority of more recent case-control and cohort studies of benzodiazepine use during pregnancy, which were adjusted for confounding exposures to alcohol, tobacco and other medications, have not confirmed these findings.

Animal Data
In a study in which clobazam (0, 150, 450, or 750 mg/kg/day) was orally administered to pregnant rats throughout the period of organogenesis, embryofetal mortality and incidences of fetal skeletal variations were increased at all doses. The low-effect dose for embryofetal developmental toxicity in rats (150 mg/kg/day) was associated with plasma exposures (AUC) for clobazam and its major active metabolite, N-desmethylclobazam, lower than those in humans at the maximum recommended human dose (MRHD) of 40 mg/day.

Oral administration of clobazam (0, 10, 30, or 75 mg/kg/day) to pregnant rabbits throughout the period of organogenesis resulted in decreased fetal body weights, and increased incidences of fetal malformations (visceral and skeletal) at the mid and high doses, and an increase in embryofetal mortality at the high dose. Incidences of fetal variations were increased at all doses. The highest dose tested was associated with maternal toxicity (ataxia and decreased activity). The low-effect dose for embryofetal developmental toxicity in rabbits (10 mg/kg/day) was associated with plasma exposures for clobazam and N-desmethylclobazam lower than those in humans at the MRHD.

Oral administration of clobazam (0, 50, 350, or 750 mg/kg/day) to rats throughout pregnancy and lactation resulted in increased embryofetal mortality at the high dose, decreased pup survival at the mid and high doses and alterations in offspring behavior (locomotor activity) at all doses. The low-effect dose for adverse effects on pre- and postnatal development in rats (50 mg/kg/day) was associated with plasma exposures for clobazam and N-desmethylclobazam lower than those in humans at the MRHD.

8.2 Lactation

Risk Summary
ONFI is excreted in human milk (see Data). There are reports of sedation, poor feeding and poor weight gain in infants exposed to benzodiazepines through breast milk. There are no data on the effects of clobazam on milk production. The developmental and health benefits of breastfeeding should be considered along with the mother’s clinical need for ONFI and any potential adverse effects on the breastfed infant from ONFI or from the underlying maternal condition.

Clinical Considerations
Adverse reactions such as somnolence and difficulty feeding have been reported in infants during breastfeeding in postmarketing experience with ONFI. Infants exposed to ONFI through breast milk should be monitored for sedation, poor feeding and poor weight gain.

Data
Scientific literature on ONFI use during lactation is limited. After short-term administration, clobazam and N-desmethylclobazam are transferred into breast milk.

8.3 Females and Males of Reproductive Potential

Administration of clobazam to rats prior to and during mating and early gestation resulted in adverse effects on fertility and early embryonic development at plasma exposures for clobazam and its major active metabolite, N-desmethylclobazam, below those in humans at the MRHD [see Nonclinical Toxicology (13.1)].

8.4 Pediatric Use

Safety and effectiveness in patients less than 2 years of age have not been established.

In a study in which clobazam (0, 4, 36, or 120 mg/kg/day) was orally administered to rats during the juvenile period of development (postnatal days 14 to 48), adverse effects on growth (decreased bone density and bone length) and behavior (altered motor activity and auditory startle response; learning deficit) were observed at the high dose. The effect on bone density, but not on behavior, was reversible when drug was discontinued. The no-effect level for juvenile toxicity (36 mg/kg/day) was associated with plasma exposures (AUC) to clobazam and its major active metabolite, N-desmethylclobazam, less than those expected at therapeutic doses in pediatric patients.

8.5 Geriatric Use

Clinical studies of ONFI did not include sufficient numbers of subjects aged 65 and over to determine whether they respond differently from younger subjects. However, elderly subjects appear to eliminate clobazam more slowly than younger subjects based on population pharmacokinetic analysis. For these reasons, the initial dose in elderly patients should be 5 mg/day. Patients should be titrated initially to 10-20 mg/day. Patients may be titrated further to a maximum daily dose of 40 mg if tolerated [see Dosage and Administration (2.4), Clinical Pharmacology (12.3)].

8.6 CYP2C19 Poor Metabolizers

Concentrations of clobazam's active metabolite, N-desmethylclobazam, are higher in CYP2C19 poor metabolizers than in extensive metabolizers. For this reason, dosage modification is recommended [see Dosage and Administration (2.5), Clinical Pharmacology (12.3)].

8.7 Renal Impairment

The pharmacokinetics of ONFI were evaluated in patients with mild and moderate renal impairment. There were no significant differences in systemic exposure (AUC and Cmax) between patients with mild or moderate renal impairment and healthy subjects. No dose adjustment is required for patients with mild and moderate renal impairment. There is essentially no experience with ONFI in patients with severe renal impairment or ESRD. It is not known if clobazam or its active metabolite, N-desmethylclobazam, is dialyzable [see Dosage and Administration (2.6), Clinical Pharmacology (12.3)].

8.8 Hepatic Impairment

ONFI is hepatically metabolized; however, there are limited data to characterize the effect of hepatic impairment on the pharmacokinetics of ONFI. For this reason, dosage adjustment is recommended in patients with mild to moderate hepatic impairment (Child-Pugh score 5-9). There is inadequate information about metabolism of ONFI in patients with severe hepatic impairment [see Dosage and Administration (2.7), Clinical Pharmacology (12.3)].

9 DRUG ABUSE AND DEPENDENCE

9.1 Controlled Substance

ONFI contains clobazam, a Schedule IV controlled substance.

9.2 Abuse

ONFI is a benzodiazepine and a CNS depressant with a potential for abuse and addiction. Abuse is the intentional, non-therapeutic use of a drug, even once, for its desirable psychological or physiological effects. Misuse is the intentional use, for therapeutic purposes, of a drug by an individual in a way other than prescribed by a health care provider or for whom it was not prescribed. Drug addiction is a cluster of behavioral, cognitive, and physiological phenomena that may include a strong desire to take the drug, difficulties in controlling drug use (e.g., continuing drug use despite harmful consequences, giving a higher priority to drug use than other activities and obligations), and possible tolerance or physical dependence. Even taking benzodiazepines as prescribed may put patients at risk for abuse and misuse of their medication. Abuse and misuse of benzodiazepines may lead to addiction.

Abuse and misuse of benzodiazepines often (but not always) involve the use of doses greater than the maximum recommended dosage and commonly involve concomitant use of other medications, alcohol, and/or illicit substances, which is associated with an increased frequency of serious adverse outcomes, including respiratory depression, overdose, or death. Benzodiazepines are often sought by individuals who abuse drugs and other substances, and by individuals with addictive disorders [see Warnings and Precautions (5.2)].

The following adverse reactions have occurred with benzodiazepine abuse and/or misuse: abdominal pain, amnesia, anorexia, anxiety, aggression, ataxia, blurred vision, confusion, depression, disinhibition, disorientation, dizziness, euphoria, impaired concentration and memory, indigestion, irritability, muscle pain, slurred speech, tremors, and vertigo.

The following severe adverse reactions have occurred with benzodiazepine abuse and/or misuse: delirium, paranoia, suicidal ideation and behavior, seizures, coma, breathing difficulty, and death. Death is more often associated with polysubstance use (especially benzodiazepines with other CNS depressants such as opioids and alcohol).

The World Health Organization epidemiology database contains reports of drug abuse, misuse, and overdoses associated with clobazam.

9.3 Dependence

Physical Dependence

ONFI may produce physical dependence from continued therapy. Physical dependence is a state that develops as a result of physiological adaptation in response to repeated drug use, manifested by withdrawal signs and symptoms after abrupt discontinuation or a significant dose reduction of a drug. Abrupt discontinuation or rapid dosage reduction of benzodiazepines or administration of flumazenil, a benzodiazepine antagonist, may precipitate acute withdrawal reactions, including seizures, which can be life-threatening. Patients at an increased risk of withdrawal adverse reactions after benzodiazepine discontinuation or rapid dosage reduction include those who take higher dosages (i.e., higher and/or more frequent doses) and those who have had longer durations of use [see Warnings and Precautions (5.3)].In clinical trials, cases of dependency were reported following abrupt discontinuation of ONFI.

To reduce the risk of withdrawal reactions, use a gradual taper to discontinue ONFI or reduce the dosage [see Dosage and Administration (2.2) and Warnings and Precautions (5.3)].

Acute Withdrawal Signs and Symptoms

Acute withdrawal signs and symptoms associated with benzodiazepines have included abnormal involuntary movements, anxiety, blurred vision, depersonalization, depression, derealization, dizziness, fatigue, gastrointestinal adverse reactions (e.g., nausea, vomiting, diarrhea, weight loss, decreased appetite), headache, hyperacusis, hypertension, irritability, insomnia, memory impairment, muscle pain and stiffness, panic attacks, photophobia, restlessness, tachycardia, and tremor. More severe acute withdrawal signs and symptoms, including life-threatening reactions, have included catatonia, convulsions, delirium tremens, depression, hallucinations, mania, psychosis, seizures, and suicidality.

Protracted Withdrawal Syndrome

Protracted withdrawal syndrome associated with benzodiazepines is characterized by anxiety, cognitive impairment, depression, insomnia, formication, motor symptoms (e.g., weakness, tremor, muscle twitches), paresthesia, and tinnitus that persists beyond 4 to 6 weeks after initial benzodiazepine withdrawal. Protracted withdrawal symptoms may last weeks to more than 12 months. As a result, there may be difficulty in differentiating withdrawal symptoms from potential re-emergence or continuation of symptoms for which the benzodiazepine was being used.

Tolerance

Tolerance to ONFI may develop from continued therapy. Tolerance is a physiological state characterized by a reduced response to a drug after repeated administration (i.e., a higher dose of a drug is required to produce the same effect that was once obtained at a lower dose). Tolerance to the therapeutic effect of ONFI may develop; however, little tolerance develops to the amnestic reactions and other cognitive impairments caused by benzodiazepines.

10 OVERDOSAGE

Overdosage of benzodiazepines is characterized by central nervous system depression ranging from drowsiness to coma. In mild to moderate cases, symptoms can include drowsiness, confusion, dysarthria, lethargy, hypnotic state, diminished reflexes, ataxia, and hypotonia. Rarely, paradoxical or disinhibitory reactions (including agitation, irritability, impulsivity, violent behavior, confusion, restlessness, excitement, and talkativeness) may occur. In severe overdosage cases, patients may develop respiratory depression and coma. Overdosage of benzodiazepines in combination with other CNS depressants (including alcohol and opioids) may be fatal [see Warnings and Precautions (5.2)]. Markedly abnormal (lowered or elevated) blood pressure, heart rate, or respiratory rate raise the concern that additional drugs and/or alcohol are involved in the overdosage.

In managing benzodiazepine overdosage, employ general supportive measures, including intravenous fluids and airway maintenance. Flumazenil, a specific benzodiazepine receptor antagonist indicated for the complete or partial reversal of the sedative effects of benzodiazepines in the management of benzodiazepine overdosage, can lead to withdrawal and adverse reactions, including seizures, particularly in the context of mixed overdosage with drugs that increase seizure risk (e.g., tricyclic and tetracyclic antidepressants) and in patients with long-term benzodiazepine use and physical dependency. The risk of withdrawal seizures with flumazenil may be increased in patients with epilepsy. Flumazenil is contraindicated in patients who have received a benzodiazepine for control of a potentially life-threatening condition (e.g., status epilepticus). If the decision is made to use flumazenil, it should be used as an adjunct to, not as a substitute for, supportive management of benzodiazepine overdosage. See the flumazenil injection Prescribing Information.

Consider contacting the Poison Help line (1-800-222-1222) or a medical toxicologist for additional overdosage management recommendations.

11 DESCRIPTION

Table 4. Description
Proprietary Name: | ONFI®
Established Name: | Clobazam
Dosage Forms: | Tablet and Oral Suspension
Route of Administration: | Oral
Established Pharmacologic Class of Drug: | Benzodiazepine
Chemical Name: | 7-Chloro-1-methyl-5-phenyl-1H-1,5 benzodiazepine-2,4(3H,5H)-dione
Structural Formula:

Clobazam is a white or almost white, crystalline powder with a slightly bitter taste; is slightly soluble in water, sparingly soluble in ethanol, and freely soluble in methylene chloride. The melting range of clobazam is from 182ºC to 185ºC. The molecular formula is C16H13O2N2Cl and the molecular weight is 300.7.

Each ONFI tablet contains 10 mg or 20 mg of clobazam. Tablets also contain as inactive ingredients: modified corn starch, lactose monohydrate, magnesium stearate, silicon dioxide, and talc.

ONFI is also available for oral administration as an off-white suspension containing clobazam at a concentration of 2.5 mg/mL. Inactive ingredients include magnesium aluminum silicate, xanthan gum, citric acid monohydrate, disodium hydrogen phosphate dihydrate, simethicone emulsion, polysorbate 80, methylparaben, propylparaben, propylene glycol, sucralose, maltitol solution, berry flavor, purified water.

12 CLINICAL PHARMACOLOGY

12.1 Mechanism of Action

The exact mechanism of action for clobazam, a 1,5-benzodiazepine, is not fully understood but is thought to involve potentiation of GABAergic neurotransmission resulting from binding at the benzodiazepine site of the GABAA receptor.

12.2 Pharmacodynamics

Effects on Electrocardiogram
The effect of ONFI 20 mg and 80 mg administered twice daily on QTc interval was evaluated in a randomized, evaluator-blinded, placebo-, and active-controlled (moxifloxacin 400 mg) parallel thorough QT study in 280 healthy subjects. In a study with demonstrated ability to detect small effects, the upper bound of the one-sided 95% confidence interval for the largest placebo-adjusted, baseline-corrected QTc based on the Fridericia correction method was below 10 ms, the threshold for regulatory concern. Thus, at a dose two times the maximum recommended dose, ONFI did not prolong the QTc interval to any clinically relevant extent.

12.3 Pharmacokinetics

The peak plasma levels (Cmax) and the area under the curve (AUC) of clobazam are dose-proportional over the dose range of 10-80 mg following single- or multiple-dose administration of ONFI. Based on a population pharmacokinetic analysis, the pharmacokinetics of clobazam are linear from 5-160 mg/day. Clobazam is converted to N-desmethylclobazam which has about 1/5 the activity of clobazam. The estimated mean elimination half-lives (t1/2) of clobazam and N-desmethylclobazam were 36-42 hours and 71-82 hours, respectively.

Absorption
Clobazam is rapidly and extensively absorbed following oral administration. The time to peak concentrations (Tmax) of clobazam tablets under fasted conditions ranged from 0.5 to 4 hours after single- or multiple-dose administrations. The relative bioavailability of clobazam tablets compared to an oral solution is approximately 100%. After single dose administration of the oral suspension under fasted conditions, the Tmax ranged from 0.5 to 2 hours. Based on exposure (Cmax and AUC) of clobazam, ONFI tablets and suspension were shown to have similar bioavailability under fasted conditions. The administration of ONFI tablets with food or when crushed in applesauce does not affect absorption. Although not studied, the oral bioavailability of the oral suspension is unlikely to be affected under fed conditions.

Distribution
Clobazam is lipophilic and distributes rapidly throughout the body. The apparent volume of distribution at steady state was approximately 100 L. The in vitro plasma protein binding of clobazam and N-desmethylclobazam is approximately 80-90% and 70%, respectively.

Metabolism and Excretion
Clobazam is extensively metabolized in the liver, with approximately 2% of the dose recovered in urine and 1% in feces as unchanged drug. The major metabolic pathway of clobazam involves N-demethylation, primarily by CYP3A4 and to a lesser extent by CYP2C19 and CYP2B6. N-desmethylclobazam, an active metabolite, is the major circulating metabolite in humans, and at therapeutic doses, plasma concentrations are 3-5 times higher than those of the parent compound. Based on animal and in vitro receptor binding data, estimates of the relative potency of N-desmethylclobazam compared to parent compound range from 1/5 to equal potency. N-desmethylclobazam is extensively metabolized, mainly by CYP2C19. N-desmethylclobazam and its metabolites comprise ~94% of the total drug-related components in urine. Following a single oral dose of radiolabeled drug, approximately 11% of the dose was excreted in the feces and approximately 82% was excreted in the urine.

The polymorphic CYP2C19 is the major contributor to the metabolism of the pharmacologically active N-desmethylclobazam [see Clinical Pharmacology (12.5)]. In CYP2C19 poor metabolizers, levels of N-desmethylclobazam were 5-fold higher in plasma and 2- to 3-fold higher in the urine than in CYP2C19 extensive metabolizers.

Pharmacokinetics in Specific Populations
Age
Population pharmacokinetic analyses showed that the clearance of clobazam is lower in elderly subjects compared to other age groups (ages 2 to 64). Dosing should be adjusted in the elderly [see Dosage and Administration (2.4)].

Sex
Population pharmacokinetic analyses showed no difference in the clearance of clobazam between women and men.

Race
Population pharmacokinetic analyses including Caucasian (75%), African American (15%), and Asian (9%) subjects showed that there is no evidence of clinically significant effect of race on the clearance of clobazam.

Renal Impairment
The effect of renal impairment on the pharmacokinetics of clobazam was evaluated in patients with mild (creatinine clearance [CLCR] >50 to 80 mL/min; N=6) and moderate (CLCR=30 to 50 mL/min; N=6) renal dysfunction, with matching healthy controls (N=6), following administration of multiple doses of ONFI 20 mg/day. There were insignificant changes in Cmax (3-24%) and AUC (≤13%) for clobazam or N-desmethylclobazam in patients with mild or moderate renal impairment compared to patients with normal renal function. Patients with severe renal impairment or ESRD were not included in this study.

Hepatic Impairment
There are limited data to characterize the effect of hepatic impairment on the pharmacokinetics of clobazam. In a small study, the pharmacokinetics of a 20 mg single oral dose of ONFI in 9 patients with liver impairment were compared to healthy controls (N=6). The Cmax and the mean plasma clearance of clobazam, as well as the Cmax of N-desmethylclobazam, showed no significant change compared to the healthy controls. The AUC values of N-desmethylclobazam in these patients were not available. Adjust dosage in patients with hepatic impairment [see Dosage and Administration (2.7)].

Drug Interaction Studies

In vitro studies:
Clobazam did not inhibit CYP1A2, CYP2C8, CYP2C9, CYP2C19, CYP2D6, CYP3A4, UGT1A1, UGT1A4, UGT1A6, or UGT2B4 in vitro. N-desmethylclobazam showed weak inhibition of CYP2C9, UGT1A4, UGT1A6 and UGT2B4.

Clobazam and N-desmethylclobazam did not significantly increase CYP1A2 or CYP2C19 activities, but did induce CYP3A4 activity in a concentration-dependent manner. Clobazam and N-desmethylclobazam also increased UGT1A1 mRNA but at concentrations much higher than therapeutic levels. The potential for clobazam or N-desmethylclobazam to induce CYP2B6 and CYP2C8 has not been evaluated.

Clobazam and N-desmethylclobazam do not inhibit P-glycoprotein (P-gp), but are P-gp substrates.

In vivo studies:

Potential for ONFI to Affect Other Drugs
The effect of repeated 40 mg once-daily doses of ONFI on the pharmacokinetic profiles of single-dose dextromethorphan (CYP2D6 substrate), midazolam (CYP3A4 substrate), caffeine (CYP1A2 substrate), and tolbutamide (CYP2C9 substrate), was studied when these probe substrates were given as a drug cocktail (N=18).

Clobazam increased AUC and Cmax of dextromethorphan by 90% and 59%, respectively, reflecting its inhibition of CYP2D6 in vivo. Drugs metabolized by CYP2D6 may require dose adjustment when used with ONFI.

Clobazam decreased the AUC and Cmax of midazolam by 27% and 24%, respectively, and increased the AUC and Cmax of the metabolite 1-hydroxymidazolam by 4-fold and 2-fold, respectively. This level of induction does not call for dosage adjustment of drugs that are primarily metabolized by CYP3A4 when used concomitantly with ONFI. Some hormonal contraceptives are metabolized by CYP3A4 and their effectiveness may be diminished when given with ONFI [see Drug Interactions (7.3)]. Repeated ONFI doses had no effect on caffeine and tolbutamide.

A population pharmacokinetic analysis indicated clobazam did not affect the exposure of valproic acid (a CYP2C9/2C19 substrate) or lamotrigine (a UGT substrate).

Potential for Other Drugs to Affect ONFI
Co-administration of ketoconazole (a strong CYP3A4 inhibitor) 400 mg once-daily for 5 days increased clobazam AUC by 54%, with an insignificant effect on clobazam Cmax. There was no significant change in AUC and Cmax of N-desmethylclobazam (N=18).

Strong (e.g., fluconazole, fluvoxamine, ticlopidine) and moderate (e.g., omeprazole) inhibitors of CYP2C19 may result in up to a 5-fold increase in exposure to N-desmethylclobazam, the active metabolite of clobazam, based on extrapolation from pharmacogenomic data [see Clinical Pharmacology (12.5)]. Dosage adjustment of ONFI may be necessary when co-administered with strong or moderate CYP2C19 inhibitors [see Drug Interactions (7.4)].

The effects of concomitant antiepileptic drugs that are CYP3A4 inducers (phenobarbital, phenytoin, and carbamazepine), CYP2C19 inducers (valproic acid, phenobarbital, phenytoin, and carbamazepine), and CYP2C19 inhibitors (felbamate and oxcarbazepine) were evaluated using data from clinical trials. Results of population pharmacokinetic analysis show that these concomitant antiepileptic drugs did not significantly alter the pharmacokinetics of clobazam or N-desmethylclobazam at steady-state.

Alcohol has been reported to increase the maximum plasma exposure of clobazam by approximately 50%. Alcohol may have additive CNS depressant effects when taken with ONFI [see Warnings and Precautions (5.4), Drug Interactions (7.2)].

12.5 Pharmacogenomics

The polymorphic CYP2C19 is the main enzyme that metabolizes the pharmacologically active N-desmethylclobazam. Compared to CYP2C19 extensive metabolizers, N-desmethylclobazam AUC and Cmax are approximately 3-5 times higher in poor metabolizers (e.g., subjects with *2/*2 genotype) and 2 times higher in intermediate metabolizers (e.g., subjects with *1/*2 genotype). The prevalence of CYP2C19 poor metabolism differs depending on racial/ethnic background. Dosage in patients who are known CYP2C19 poor metabolizers may need to be adjusted [see Dosage and Administration (2.5)].

The systemic exposure of clobazam is similar for both CYP2C19 poor and extensive metabolizers.

13 NONCLINICAL TOXICOLOGY

13.1 Carcinogenesis, Mutagenesis, Impairment of Fertility

Carcinogenesis
In mice, oral administration of clobazam (0, 6, 12, or 24 mg/kg/day) for 2 years did not result in an increase in tumors. The highest dose tested was approximately 3 times the maximum recommended human dose (MRHD) of 40 mg/day, based on body surface area (mg/m^2).

In rats, oral administration of clobazam for 2 years resulted in increases in tumors of the thyroid gland (follicular cell adenoma and carcinoma) and liver (hepatocellular adenoma) at the mid and high doses. The low dose, not associated with an increase in tumors, was associated with plasma exposures (AUC) for clobazam and its major active metabolite, N-desmethylclobazam, less than that in humans at the MRHD.

Mutagenesis
Clobazam and the major active metabolite, N-desmethylclobazam, were negative for genotoxicity, based on data from a battery of in vitro (bacteria reverse mutation, mammalian clastogenicity) and in vivo (mouse micronucleus) assays.

Impairment of Fertility
In a fertility study in which clobazam (50, 350, or 750 mg/kg/day, corresponding to 12, 84 and 181 times the oral Maximum Recommended Human Dose, MRHD, of 40 mg/day based on mg/m^2 body surface) was orally administered to male and female rats prior to and during mating and continuing in females to gestation day 6, increases in abnormal sperm and pre-implantation loss were observed at the highest dose tested. The no-effect level for fertility and early embryonic development in rats was associated with plasma exposures (AUC) for clobazam and its major active metabolite, N-desmethylclobazam, less than those in humans at the maximum recommended human dose of 40 mg/day.

14 CLINICAL STUDIES

The effectiveness of ONFI for the adjunctive treatment of seizures associated with Lennox-Gastaut syndrome was established in two multicenter controlled studies (Study 1 and Study 2). Both studies were similar in terms of disease characteristics and concomitant AED treatments. The most common concomitant AED treatments at baseline included: valproate, lamotrigine, levetiracetam, and topiramate.

Study 1
Study 1 (N=238) was a randomized, double-blind, placebo-controlled study consisting of a 4-week baseline period followed by a 3-week titration period and 12-week maintenance period. Patients age 2-54 years with a current or prior diagnosis of LGS were stratified into 2 weight groups (12.5 kg to ≤30 kg or >30 kg) and then randomized to placebo or one of three target maintenance doses of ONFI according to Table 5.

Table 5. Study 1 Total Daily Dose
 | ≤30 kg Body Weight | >30 kg Body Weight
Low Dose | 5 mg daily | 10 mg daily
Medium Dose | 10 mg daily | 20 mg daily
High Dose | 20 mg daily | 40 mg daily

Doses above 5 mg/day were administered in two divided doses.

The primary efficacy measure was the percent reduction in the weekly frequency of drop seizures (atonic, tonic, or myoclonic), also known as drop attacks, from the 4-week baseline period to 12-week maintenance period.

The pre-dosing baseline mean weekly drop seizure frequency was 98, 100, 61, and 105 for the placebo, low-, medium-, and high-dose groups, respectively. Figure 1 presents the mean percent reduction in weekly drop seizures from this baseline. All dose groups of ONFI were statistically superior (p≤0.05) to the placebo group. This effect appeared to be dose dependent.

Figure 1. Mean Percent Reduction from Baseline in Weekly Drop Seizure Frequency (Study 1)

Figure 2 shows changes from baseline in weekly drop seizure frequency by category for patients treated with ONFI and placebo in Study 1. Patients in whom the seizure frequency increased are shown at left as "worse." Patients in whom the seizure frequency decreased are shown in five categories.

Figure 2. Drop Seizure Response by Category for ONFI and Placebo (Study 1)

There was no evidence that tolerance to the therapeutic effect of ONFI developed during the 3-month maintenance period.

Study 2
Study 2 (N=68) was a randomized, double-blind comparison study of high- and low-dose ONFI, consisting of a 4-week baseline period followed by a 3-week titration period and 4-week maintenance period. Patients age 2-25 years with a current or prior diagnosis of LGS were stratified by weight, then randomized to either a low or high dose of ONFI, and then entered a 3-week titration period.

The primary efficacy measure was the percent reduction in the weekly frequency of drop seizures (atonic, tonic, or myoclonic), also known as drop attacks, from the 4-week baseline period to the 4-week maintenance period.

A statistically significantly greater reduction in seizure frequency was observed in the high-dose group compared to the low-dose group (median percent reduction of 93% vs 29%; p<0.05).

16 HOW SUPPLIED/STORAGE AND HANDLING

Each ONFI tablet contains 10 mg or 20 mg of clobazam and is a white to off-white, oval tablet with a functional score on one side and either a "1" and "0" or a "2" and "0" debossed on the other side.

NDC 67386-314-01: 10 mg scored tablet, Bottles of 100
NDC 67386-315-01: 20 mg scored tablet, Bottles of 100

ONFI oral suspension is a berry flavored off-white liquid supplied in a bottle with child-resistant closure. The oral suspension is packaged with a dispenser set which contains two calibrated oral dosing syringes and a bottle adapter.

Store and dispense ONFI oral suspension in its original bottle in an upright position. Use within 90 days of first opening the bottle, then discard any remainder.

NDC 67386-313-21: 2.5 mg/mL supplied in a bottle containing 120 mL of suspension.

Store tablets and oral suspension at 20°C to 25°C (68°F to 77°F). See USP controlled room temperature.

17 PATIENT COUNSELING INFORMATION

Advise the patient to read the FDA-approved patient labeling (Medication Guide and Instructions for Use).

Risks from Concomitant Use with Opioids

Inform patients and caregivers that potentially fatal additive effects may occur if ONFI is used with opioids and not to use such drugs concomitantly unless supervised by a healthcare provider [see Warnings and Precautions (5.1), Drug Interactions (7.1)].

Abuse, Misuse, and Addiction

Inform patients that the use of ONFI, even at recommended dosages, exposes users to risks of abuse, misuse, and addiction, which can lead to overdose and death, especially when used in combination with other medications (e.g., opioid analgesics), alcohol, and/or illicit substances. Inform patients about the signs and symptoms of benzodiazepine abuse, misuse, and addiction; to seek medical help if they develop these signs and/or symptoms; and on the proper disposal of unused drug [see Warnings and Precautions (5.2) and Drug Abuse and Dependence (9.2)].

Withdrawal Reactions

Advise patients or caregivers that abrupt withdrawal of AEDs may increase their risk of seizure. Inform patients that the continued use of ONFI may lead to clinically significant physical dependence and that abrupt discontinuation or rapid dosage reduction of ONFI may precipitate acute withdrawal reactions, which can be life-threatening. Inform patients that in some cases, patients taking benzodiazepines have developed a protracted withdrawal syndrome with withdrawal symptoms lasting weeks to more than 12 months. Instruct patients that discontinuation or dosage reduction of ONFI may require a slow taper [see Warnings and Precautions (5.3) and Drug Abuse and Dependence (9.3)].

Somnolence or Sedation

Advise patients or caregivers to check with their healthcare provider before ONFI is taken with other CNS depressants such as other benzodiazepines, opioids, tricyclic antidepressants, sedating antihistamines, or alcohol [see Warnings and Precautions (5.4, 5.5)].

If applicable, caution patients about operating hazardous machinery, including automobiles, until they are reasonably certain that ONFI does not affect them adversely (e.g., impair judgment, thinking or motor skills).

Hypersensitivity

Inform patients or caregivers that ONFI is contraindicated in patients with a history of hypersensitivity to the drug or its ingredients [see Warnings and Precautions (5.6)].

Interactions with Hormonal Contraceptives
Counsel women to also use non-hormonal methods of contraception when ONFI is used with hormonal contraceptives and to continue these alternative methods for 28 days after discontinuing ONFI to ensure contraceptive reliability [see Drug Interactions (7.3), Clinical Pharmacology (12.3)].

Serious Dermatological Reactions
Advise patients or caregivers that serious skin reactions have been reported in patients taking ONFI. Serious skin reactions, including SJS/TEN, may need to be treated in a hospital and may be life-threatening. If a skin reaction occurs while taking ONFI, patients or caregivers should consult with healthcare providers immediately [see Warnings and Precautions (5.6)].

DRESS/Multiorgan Hypersensitivity

Instruct patients and caregivers that a fever or rash associated with signs of other organ system involvement (e.g., lymphadenopathy, hepatic dysfunction) may be drug-related and should be reported to their healthcare provider immediately. ONFI should be discontinued immediately if a serious hypersensitivity reaction is suspected [see Warnings and Precautions (5.7)].

Suicidal Thinking and Behavior
Counsel patients, their caregivers, and their families that AEDs, including ONFI, may increase the risk of suicidal thoughts and behavior and advise them of the need to be alert for the emergence or worsening of symptoms of depression, any unusual changes in mood or behavior, or the emergence of suicidal thoughts, behavior, or thoughts of self-harm. Patients should report behaviors of concern immediately to healthcare providers [see Warnings and Precautions (5.8)].

Pregnancy
Advise pregnant females that the use of ONFI late in pregnancy can result in sedation (respiratory depression, lethargy, hypotonia) and/or withdrawal symptoms (hyperreflexia, irritability, restlessness, tremors, inconsolable crying, and feeding difficulties) in newborns [see Warnings and Precautions (5.9) and Use in Specific Populations (8.1)]. Instruct patients to notify their healthcare provider if they are pregnant.

Encourage patients to enroll in the North American Antiepileptic Drug (NAAED) Pregnancy Registry if they become pregnant while taking ONFI. The registry is collecting information about the safety of antiepileptic drugs during pregnancy [see Use in Specific Populations (8.1)].

Lactation
Counsel patients that clobazam, the active ingredient in ONFI, is excreted in breast milk. Instruct patients to notify their healthcare provider if they are breastfeeding or intend to breastfeed. Instruct breastfeeding patients who have been administered ONFI to observe their infants for sedation, poor feeding and poor weight gain, and to seek medical attention if they notice these signs [see Use in Specific Populations (8.2)].

Tablets manufactured by: Catalent Pharma Solutions, LLC
Winchester, KY 40391, U.S.A.

Oral suspension manufactured by: Rosemont Pharmaceuticals, Ltd.
Leeds, West Yorkshire LS11 9XE, U.K.

For: Lundbeck
Deerfield, IL 60015, U.S.A.

ONFI is a registered trademark of Lundbeck

MEDICATION GUIDE
ONFI® (ON-fee)
(clobazam)
tablets and oral suspension, C-IV

What is the most important information I should know about ONFI?

- ONFI is a benzodiazepine medicine. Taking benzodiazepines with opioid medicines, alcohol, or other central nervous system (CNS) depressants (including street drugs) can cause severe drowsiness, breathing problems (respiratory depression), coma, and death. Get emergency help right away if any of the following happens:
  - shallow or slowed breathing
  - breathing stops (which may lead to the heart stopping)
  - excessive sleepiness (sedation)
  Do not drive or operate heavy machinery until you know how taking ONFI with opioids affects you.
- Risk of abuse, misuse, and addiction. There is a risk of abuse, misuse, and addiction with benzodiazepines, including ONFI, which can lead to overdose and serious side effects including coma and death.
  - Serious side effects including coma and death have happened in people who have abused or misused benzodiazepines, including ONFI. These serious side effects may also include delirium, paranoia, suicidal thoughts or actions, seizures, and difficulty breathing. Call your healthcare provider or go to the nearest hospital emergency room right away if you get any of these serious side effects.
  - You can develop an addiction even if you take ONFI as prescribed by your healthcare provider.
  - Take ONFI exactly as your healthcare provider prescribed.
  - Do not share your ONFI with other people.
  - Keep ONFI in a safe place and away from children.
- Physical dependence and withdrawal reactions. ONFI can cause physical dependence and withdrawal reactions.
  - Do not suddenly stop taking ONFI. Stopping ONFI suddenly can cause serious and life-threatening side effects, including, unusual movements, responses, or expressions, seizures, sudden and severe mental or nervous system changes, depression, seeing or hearing things that others do not see or hear, an extreme increase in activity or talking, losing touch with reality, and suicidal thoughts or actions. Call your healthcare provider or go to the nearest hospital emergency room right away if you get any of these symptoms.
  - Some people who suddenly stop benzodiazepines have symptoms that can last for several weeks to more than 12 months, including, anxiety, trouble remembering, learning, or concentrating, depression, problems sleeping, feeling like insects are crawling under your skin, weakness, shaking, muscle twitching, burning or prickling feeling in your hands, arms, legs or feet, and ringing in your ears.
  - Physical dependence is not the same as drug addiction. Your healthcare provider can tell you more about the differences between physical dependence and drug addiction.
  - Do not take more ONFI than prescribed or take ONFI for longer than prescribed.

- ONFI can make you sleepy or dizzy and can slow your thinking and motor skills.
  - Do not drive, operate heavy machinery, or do other dangerous activities until you know how ONFI affects you.
  - Do not drink alcohol or take other drugs that may make you sleepy or dizzy while taking ONFI without first talking to your healthcare provider. When taken with alcohol or drugs that cause sleepiness or dizziness, ONFI may make your sleepiness or dizziness much worse.

- Serious skin reactions have been seen when ONFI is taken with other medicines and may require stopping its use. Do not stop taking ONFI without first talking to your healthcare provider.
  - A serious skin reaction can happen at any time during your treatment with ONFI, but is more likely to happen within the first 8 weeks of treatment. These skin reactions may need to be treated right away.
  - Call your healthcare provider immediately if you have skin blisters, rash, sores in mouth, hives or any other allergic reaction.
- A serious allergic reaction that may affect your skin or other parts of your body such as your liver, kidneys, heart, or blood cells. This allergic reaction can be life-threatening and can cause death, particularly if it is not treated as early as possible. Call your healthcare provider right away if you have:
  - a skin rash
  - fever or swollen glands that do not go away
  - swelling of your face
  - shortness of breath
  - dark urine
  - yellowing of the skin or whites of the eyes

- Like other antiepileptic medicines, ONFI may cause suicidal thoughts or actions in a very small number of people, about 1 in 500.

Call your healthcare provider right away if you have any of these symptoms, especially if they are new, worse, or worry you:

- thoughts about suicide or dying
- attempts to commit suicide
- new or worse depression
- new or worse anxiety or irritability
- feeling agitated or restless
- an extreme increase in activity and talking (mania)
- trouble sleeping (insomnia)
- new or worse panic attacks
- acting aggressive, being angry or violent
- acting on dangerous impulses
- other unusual changes in behavior or mood

How can I watch for early symptoms of suicidal thoughts and actions?

- Pay attention to any changes, especially sudden changes, in mood, behaviors, thoughts, or feelings.
- Keep all follow-up visits with your healthcare provider as scheduled.

Call your healthcare provider between visits as needed, especially if you are worried about symptoms.

Stopping a seizure medicine suddenly in a patient who has epilepsy can cause seizures that will not stop (status epilepticus).

Suicidal thoughts or actions can be caused by things other than medicines. If you have suicidal thoughts or actions, your healthcare provider may check for other causes.

What is ONFI?

- ONFI is a prescription medicine used along with other medicines to treat seizures associated with Lennox-Gastaut syndrome in people 2 years of age or older.

- ONFI is a federally controlled substance (C-IV) because it contains clobazam that can be abused or lead to dependence. Keep ONFI in a safe place to prevent misuse and abuse. Selling or giving away ONFI may harm others, and is against the law. Tell your healthcare provider if you have ever abused or been dependent on alcohol, prescription medicines, or street drugs.

It is not known if ONFI is safe and effective in children less than 2 years old.

Do not take ONFI if you:

- are allergic to clobazam or any of the ingredients in ONFI. See the end of this Medication Guide for a complete list of ingredients in ONFI.

Before you take ONFI, tell your healthcare provider about all your medical conditions, including if you:

- have liver or kidney problems
- have lung problems (respiratory disease)
- have or have had depression, mood problems, or suicidal thoughts or behavior
- use birth control medicine. ONFI may cause your birth control medicine to be less effective. Talk to your healthcare provider about the best birth control method to use.
- are pregnant or plan to become pregnant.
  - Taking ONFI late in pregnancy may cause your baby to have symptoms of sedation (breathing problems, sluggishness, low muscle tone), and/or withdrawal symptoms (jitteriness, irritability, restlessness, shaking, excessive crying, feeding problems).
  - Tell your healthcare provider right away if you become pregnant or think you are pregnant while taking ONFI.
  - If you become pregnant while taking ONFI, talk to your healthcare provider about registering with the North American Antiepileptic Drug Pregnancy Registry. You can register by calling 1-888-233-2334. For more information about the registry go to http://www.aedpregnancyregistry.org. The purpose of this registry is to collect information about the safety of antiepileptic drugs during pregnancy.
- are breastfeeding or plan to breastfeed. ONFI can pass into breast milk.
  - Breastfeeding during treatment with ONFI may cause your baby to have sleepiness, feeding problems, and decreased weight gain.
  - Talk to your healthcare provider about the best way to feed your baby if you take ONFI.

Tell your healthcare provider about all the medicines you take, including prescription and over-the-counter medicines, vitamins, and herbal supplements. Taking ONFI with certain other medicines can cause side effects or affect how well ONFI or the other medicines work. Do not start or stop other medicines without talking to your healthcare provider.

How should I take ONFI?

- Take ONFI exactly as your healthcare provider tells you to take it.
- Your healthcare provider will tell you how much ONFI to take and when to take it.
- ONFI tablets can be taken whole, broken in half along the score, or crushed and mixed in applesauce.
- ONFI tablets and oral suspension can be taken with or without food.
- Shake the bottle of ONFI oral suspension well right before you take each dose.
- Measure your dose of ONFI oral suspension using the bottle adapter and dosing syringes that come with your ONFI oral suspension.
- Read the Instructions for Use at the end of this Medication Guide for information on the right way to use ONFI oral suspension.
- Your healthcare provider may change your dose if needed. Do not change your dose of ONFI without talking to your healthcare provider.
- Do not stop taking ONFI without first talking to your healthcare provider.
- Stopping ONFI suddenly can cause serious problems.
- If you take too much ONFI, call your healthcare provider or go to the nearest hospital emergency room right away.

What should I avoid while taking ONFI?

See “What is the most important information I should know about ONFI?”

What are the possible side effects of ONFI?

ONFI may cause serious side effects, including: See "What is the most important information I should know about ONFI?"

The most common side effects of ONFI include:

- sleepiness
- drooling
- constipation
- cough
- pain with urination
- fever
- acting aggressive, being angry, or violent
- difficulty sleeping
- slurred speech
- tiredness
- problems with breathing

These are not all the possible side effects of ONFI. Call your doctor for medical advice about side effects. You may report side effects to FDA at 1-800-FDA-1088.

How should I store ONFI?

- Store ONFI tablets and oral suspension at room temperature between 68°F to 77°F (20°C to 25°C).

Tablets

- Keep ONFI tablets in a dry place.

Oral Suspension

- Replace the cap securely after opening.
- Store and dispense the oral suspension in its original bottle in an upright position. Use ONFI oral suspension within 90 days of first opening the bottle.
- After 90 days safely throw away any ONFI oral suspension that has not been used.
- Keep ONFI and all medicines out of the reach of children.

General Information about the safe and effective use of ONFI.

Medicines are sometimes prescribed for purposes other than those listed in a Medication Guide. Do not use ONFI for a condition for which it was not prescribed. Do not give ONFI to other people, even if they have the same symptoms that you have. It may harm them. You can ask your pharmacist or healthcare provider for information about ONFI that is written for health professionals.

What are the ingredients in ONFI?

Tablets
Active ingredient: clobazam
Inactive ingredients: modified corn starch, lactose monohydrate, magnesium stearate, silicon dioxide, and talc.

Oral Suspension
Active ingredient: clobazam
Inactive ingredients: magnesium aluminum silicate, xanthan gum, citric acid monohydrate, disodium hydrogen phosphate dihydrate, simethicone emulsion, polysorbate 80, methylparaben, propylparaben, propylene glycol, sucralose, maltitol solution, berry flavor, purified water.

Marketed by: Lundbeck, Deerfield, IL 60015, U.S.A.

ONFI is a registered trademark of Lundbeck

For more information about ONFI, go to www.ONFI.com or call Lundbeck at 1-866-402-8520.

This Medication Guide has been approved by the U.S. Food and Drug Administration Revised: 3/2024

Instructions for Use
ONFI® (ON-fee) (clobazam)
Oral Suspension, CIV

Read this Instructions for Use before using ONFI oral suspension and each time you get a refill. There may be new information. This leaflet does not take the place of talking with your healthcare provider about your medical condition or treatment.

Prepare ONFI Oral Suspension Dose
You will need the following supplies: See Figure A

- ONFI oral suspension bottle
- Bottle adapter
- Oral dosing syringe (2 dosing syringes are included in the ONFI oral suspension box).
- Use only 1 syringe to take your dose of ONFI oral suspension. If you lose or damage the syringe, or cannot read the markings, use the other syringe.

Figure A

Step 1. Remove the ONFI oral suspension bottle, bottle adapter, and 1 syringe from the box.

Step 2. Shake the bottle well before each use. See Figure B

Figure B

Step 3. Uncap the bottle and firmly insert the bottle adapter into the bottle until the adapter top is even with the bottle top. See Figure C

Figure C

Once the bottle adapter is in place, it should not be removed.

Step 4. Check your dose in milliliters (mL) as prescribed by your healthcare provider. Find this number on the syringe. Do not take more than the prescribed total dose in 1 day. See Figure D

Figure D

Step 5. Push the plunger all the way down and then insert the syringe into the upright bottle through the opening in the bottle adapter. See Figure E

Figure E

Step 6. With the syringe in place, turn the bottle upside down. Pull the plunger to the number of mLs needed (the amount of liquid medicine in Step 4). See Figure F

Figure F

Measure the mLs of medicine using the black ring on the white plunger. See Figure G

Figure G

Step 7. Remove the syringe from the bottle adapter. Slowly squirt ONFI oral suspension directly into the corner of your mouth or your child's mouth until all of the liquid medicine in the syringe is given. See Figure H

Figure H

Step 8. Cap the bottle tightly with the adapter in place. If the cap does not fit securely, check to see if the adapter is fully inserted. See Figure I

- Store and dispense ONFI oral suspension in its original bottle in an upright position at 68°F to 77°F (20°C to 25°C).
- Use ONFI oral suspension within 90 days of first opening bottle.
- After 90 days safely throw away any ONFI oral suspension that has not been used.

Figure I

Step 9. Wash the oral syringe after each use.

- To clean the oral syringe, take apart by removing the plunger completely. Pull plunger straight out of the barrel.
- The barrel and plunger can be washed with soap and water, rinsed, and allowed to dry.
- Do not wash the oral syringe in the dishwasher.

This Instruction for Use has been approved by the U.S. Food and Drug Administration.

Marketed by: Lundbeck, Deerfield, IL 60015, U.S.A.

ONFI is a registered trademark of Lundbeck

12/2016

PACKAGE LABEL

PRINCIPAL DISPLAY PANEL - 10 MG TABLET SCORED

NDC 67386-314-01

100 Tablets

Onfi®
(clobazam) Tablets

10 mg C-IV

DISPENSE THE ENCLOSED MEDICATION GUIDE WITH EACH PRESCRIPTION.

Rx only

PACKAGE LABEL

PRINCIPAL DISPLAY PANEL - 20 MG TABLET SCORED

NDC 67386-315-01

100 Tablets

Onfi®
(clobazam) Tablets

20 mg C-IV

DISPENSE THE ENCLOSED MEDICATION GUIDE WITH EACH PRESCRIPTION.

Rx only

PACKAGE LABEL

PRINCIPAL DISPLAY PANEL - 2.5 MG/ML ORAL SUSPENSION

NDC 67386-313-21

120 mL

Onfi® (clobazam)
Oral Suspension

2.5 mg/mL C-IV

FOR ORAL ADMINISTRATION ONLY.

DISPENSE THE ENCLOSED MEDICATION GUIDE AND INSTRUCTIONS FOR USE WITH EACH PRESCRIPTION.

Rx only